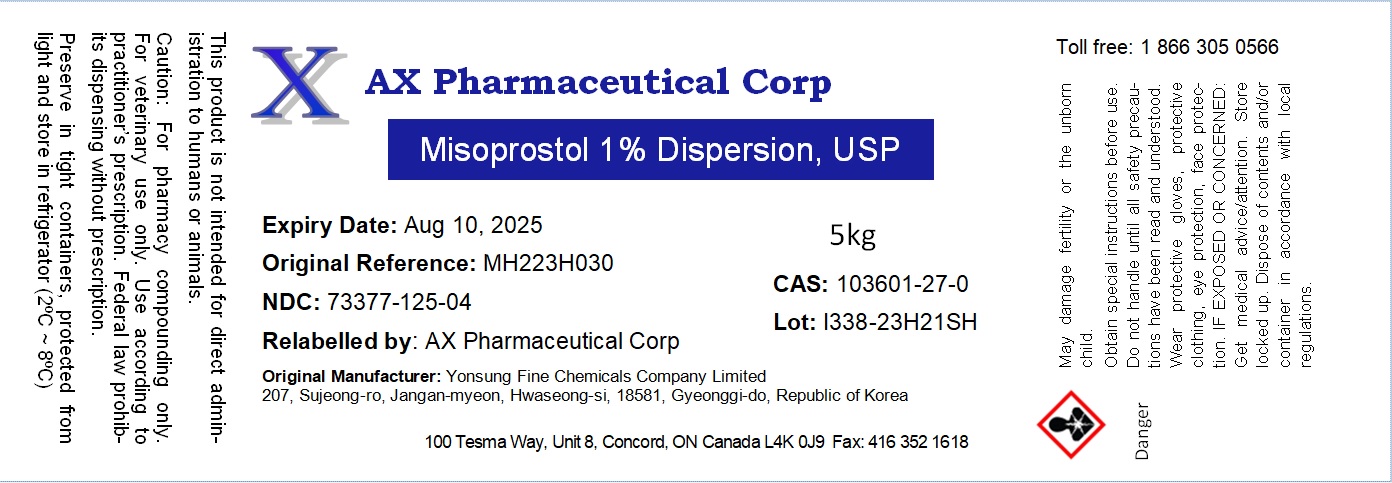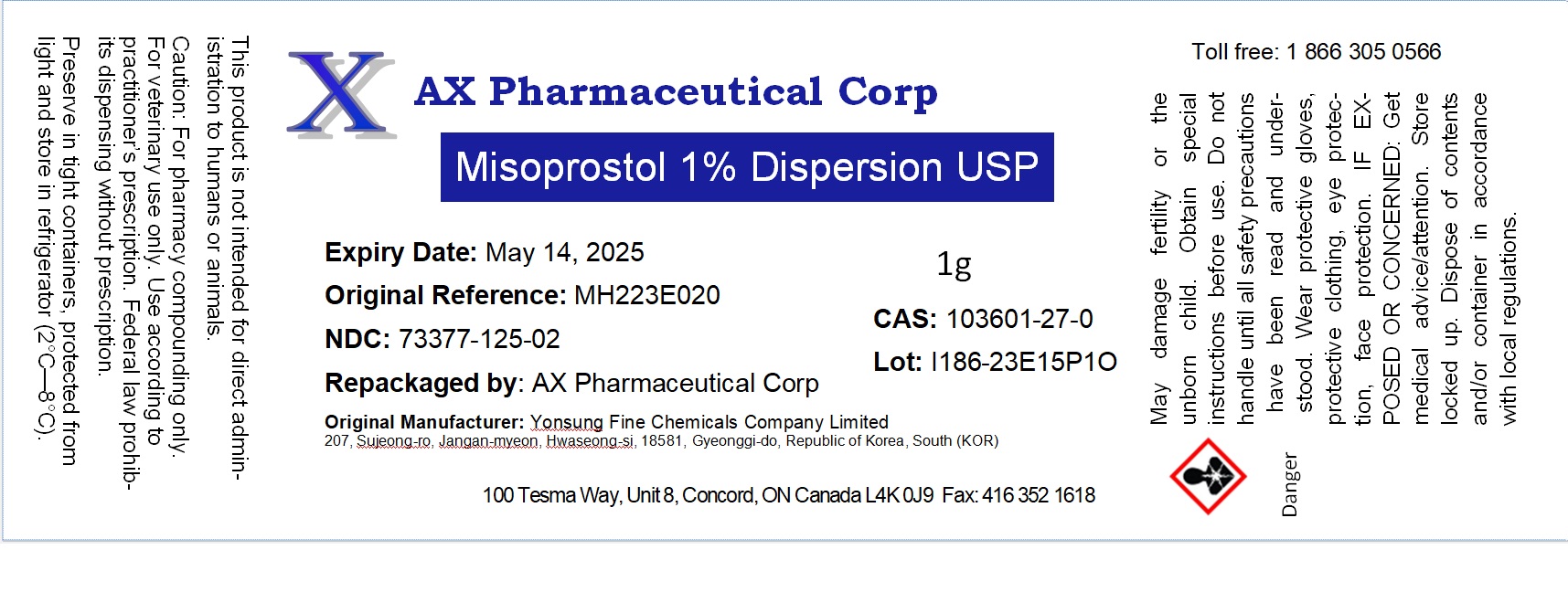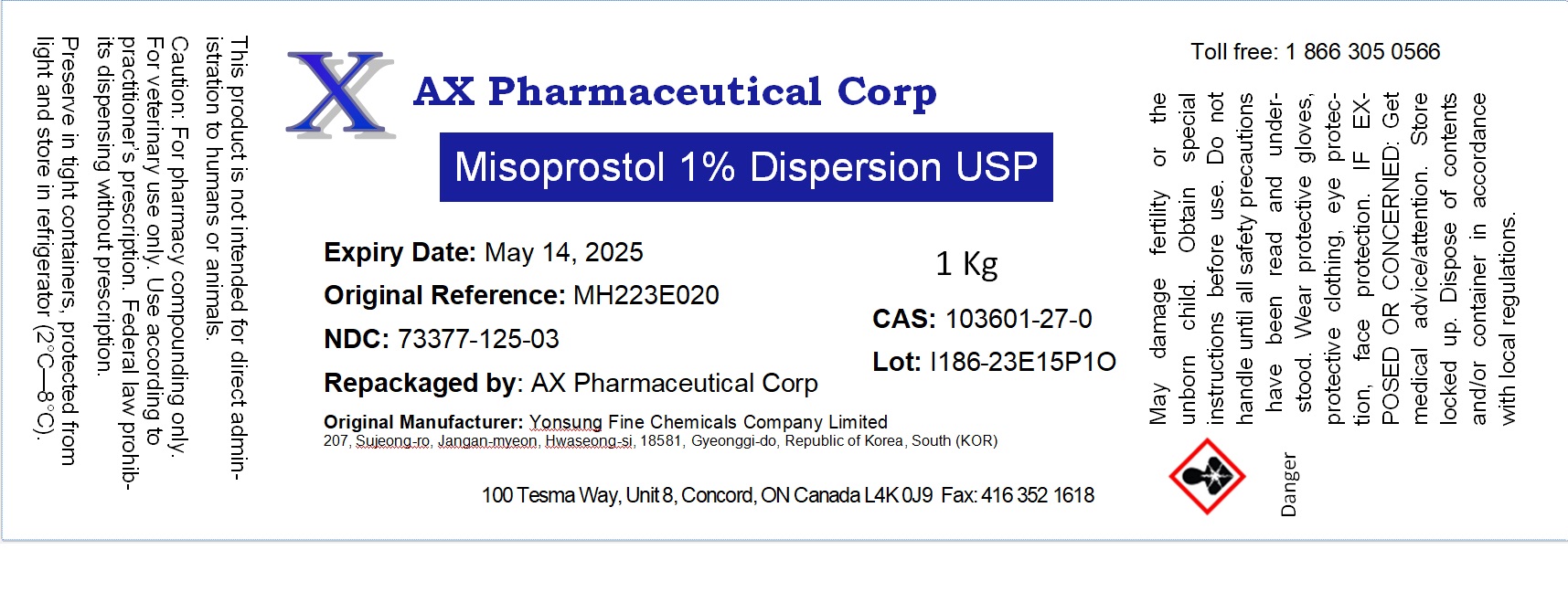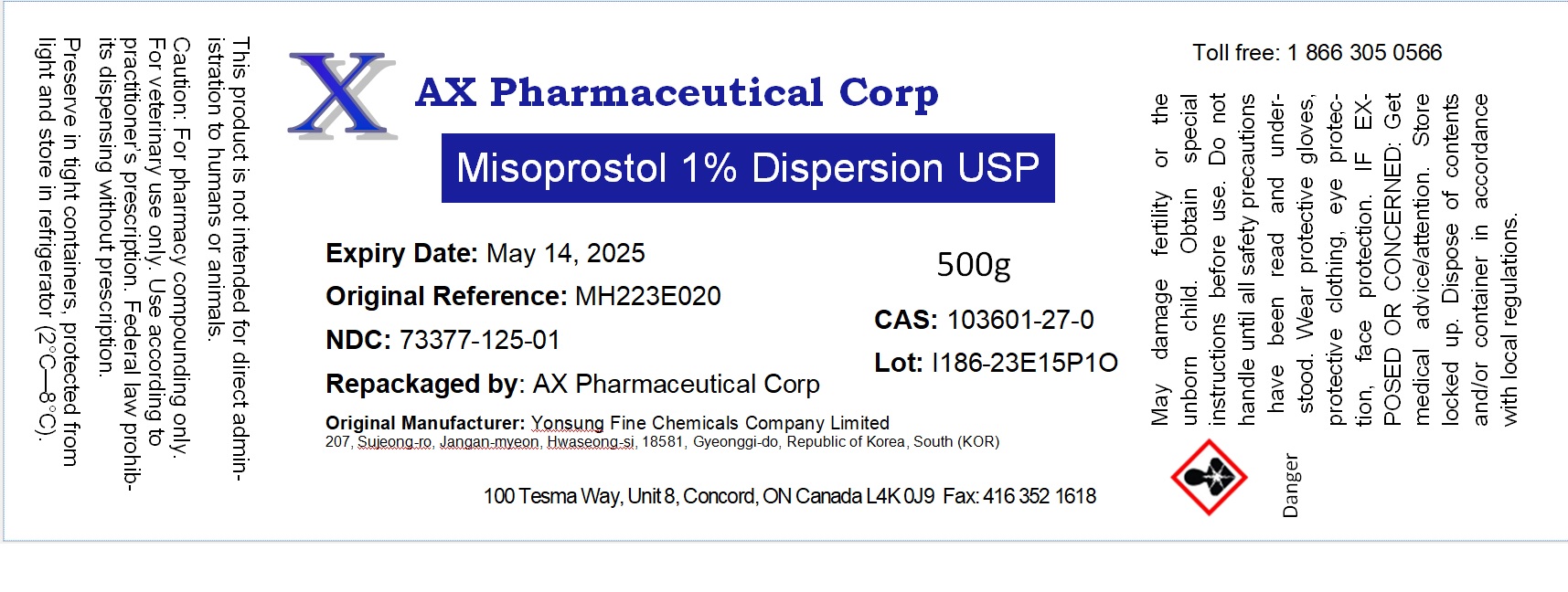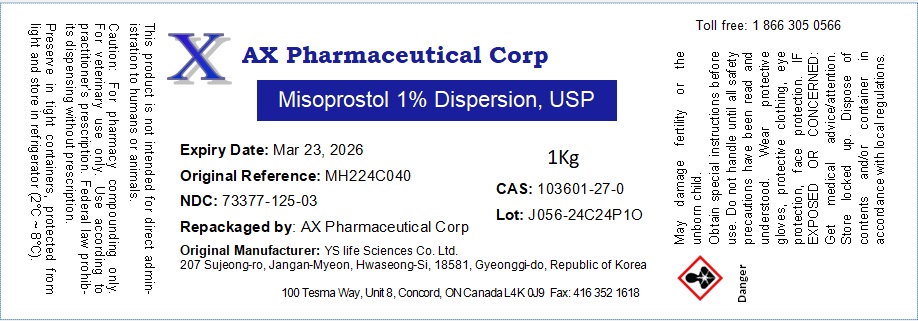 DRUG LABEL: Misoprostol 1% Dispersion
NDC: 73377-125 | Form: POWDER
Manufacturer: AX Pharmaceutical Corp
Category: other | Type: BULK INGREDIENT - ANIMAL DRUG
Date: 20240704

ACTIVE INGREDIENTS: MISOPROSTOL 1 g/1 g

Misoprostol 1% Dispersion